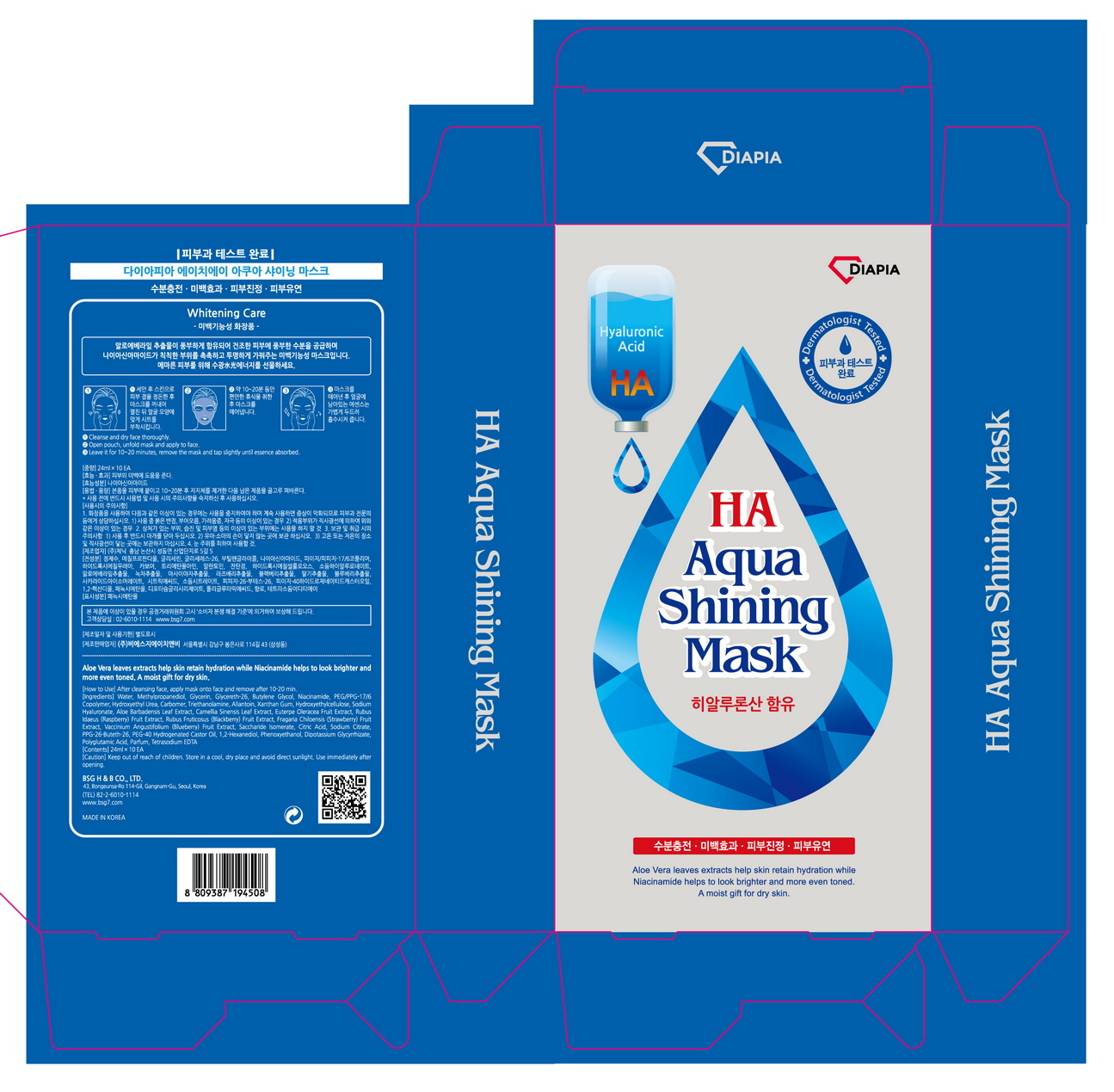 DRUG LABEL: DIAPIA HA Aqua Shining Mask
NDC: 71857-0004 | Form: LIQUID
Manufacturer: BSG H & B Co., Ltd.
Category: otc | Type: HUMAN OTC DRUG LABEL
Date: 20171114

ACTIVE INGREDIENTS: GLYCERIN 5 g/100 mL
INACTIVE INGREDIENTS: BUTYLENE GLYCOL; ALLANTOIN; WATER

ACTIVE INGREDIENT

glycerin

PURPOSE

wrinkle care

Keep out of reach of children

INDICATIONS AND USAGE

1. Cleanse and dry face thoroughly.
2. Open pouch, unfold mask and apply to face.
3. Leave it for 10 - 20 minutes, remove the mask and tap slightly until essence absorbed.

Keep out of reach of children.
Store in a cool, dry place and avoid direct sunlight.
Use immediately after opening

INACTIVE INGREDIENT

water butylene glycol, algin, allantoin, etc

DOSAGE AND ADMINISTRATION

for external use only